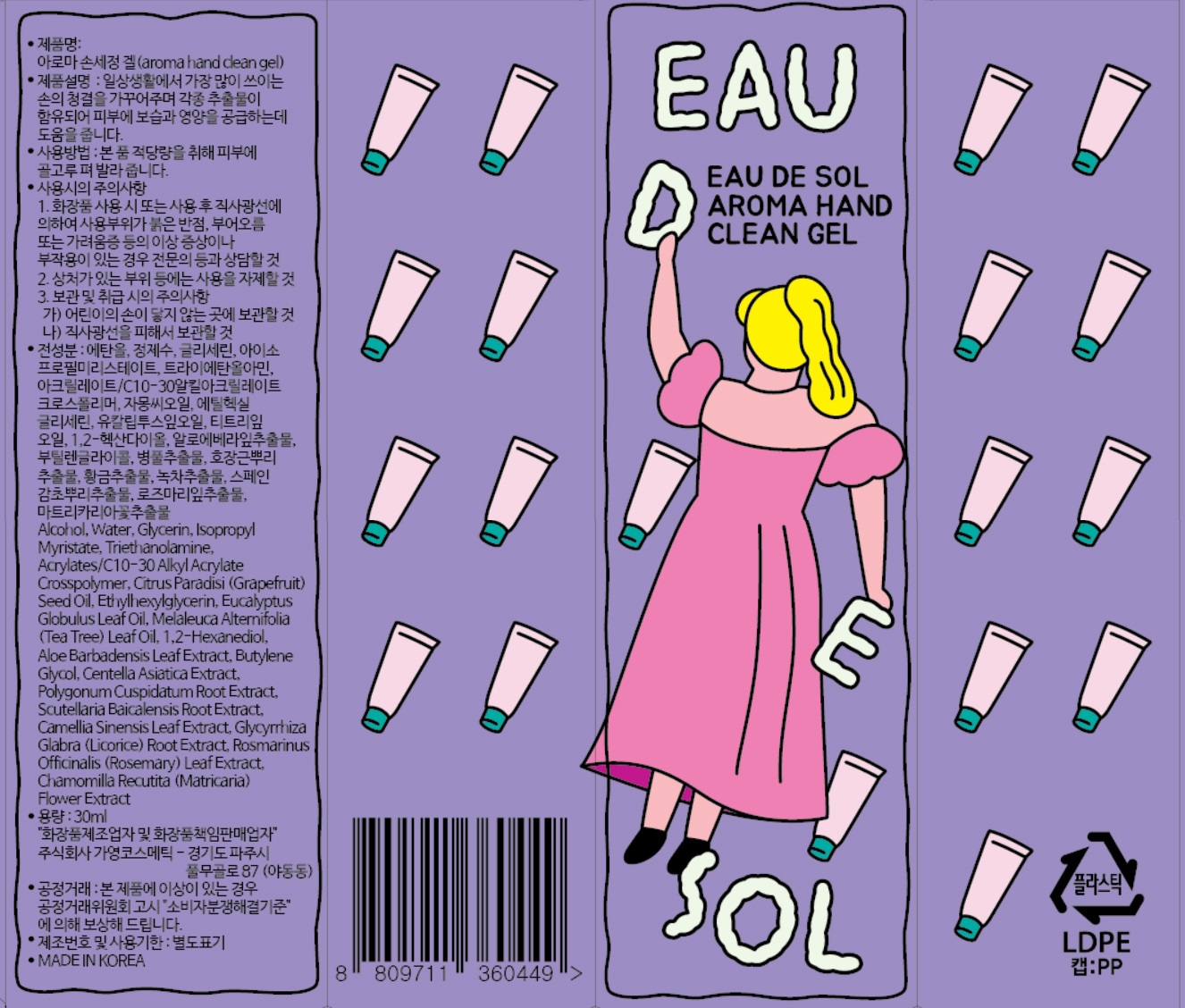 DRUG LABEL: EAU DE SOL HAND CLEAN gel
NDC: 81364-0001 | Form: GEL
Manufacturer: Good Attitude
Category: otc | Type: HUMAN OTC DRUG LABEL
Date: 20201222

ACTIVE INGREDIENTS: ALCOHOL 60 mL/100 mL
INACTIVE INGREDIENTS: GLYCERIN; WATER

Drug Facts

ACTIVE INGREDIENT

alcohol

PURPOSE

sterilization, disinfection

KEEP OUT OF REACH OF THE CHILDREN

INDICATIONS AND USAGE

take appropriate amount where needed

WARNINGS

■ Flammable. Keep away from fire or flame.

■ For external use only.

■ Do not use in eyes.

■ lf swallowed, get medical help promptly.

■ Stop use, ask doctor lf irritation occurs.

■ Keep out of reach of children.

DOSAGE AND ADMINISTRATION

for external use only

INACTIVE INGREDIENT

Alcohol, Water, Glycerin, Isopropyl Myristate, Triethanolamine, Acrylates/C10-30 Alkyl Acrylate Crosspolymer, Citrus Paradisi (Grapefruit) Seed Oil, Ethylhexylglycerin, Eucalyptus Globulus Leaf Oil, Melaleuca Alternifolia (Tea Tree) Leaf Oil, 1,2-Hexanediol, Aloe Barbadensis Leaf Extract, Butylene Glycol, Centella Asiatica Extract, Polygonum Cuspidatum Root Extract, Scutellaria Baicalensis Root Extract, Camellia Sinensis Leaf Extract, Glycyrrhiza Glabra (Licorice) Root Extract, Rosmarinus Officinalis (Rosemary) Leaf Extract, Chamomilla Recutita (Matricaria) Flower Extract